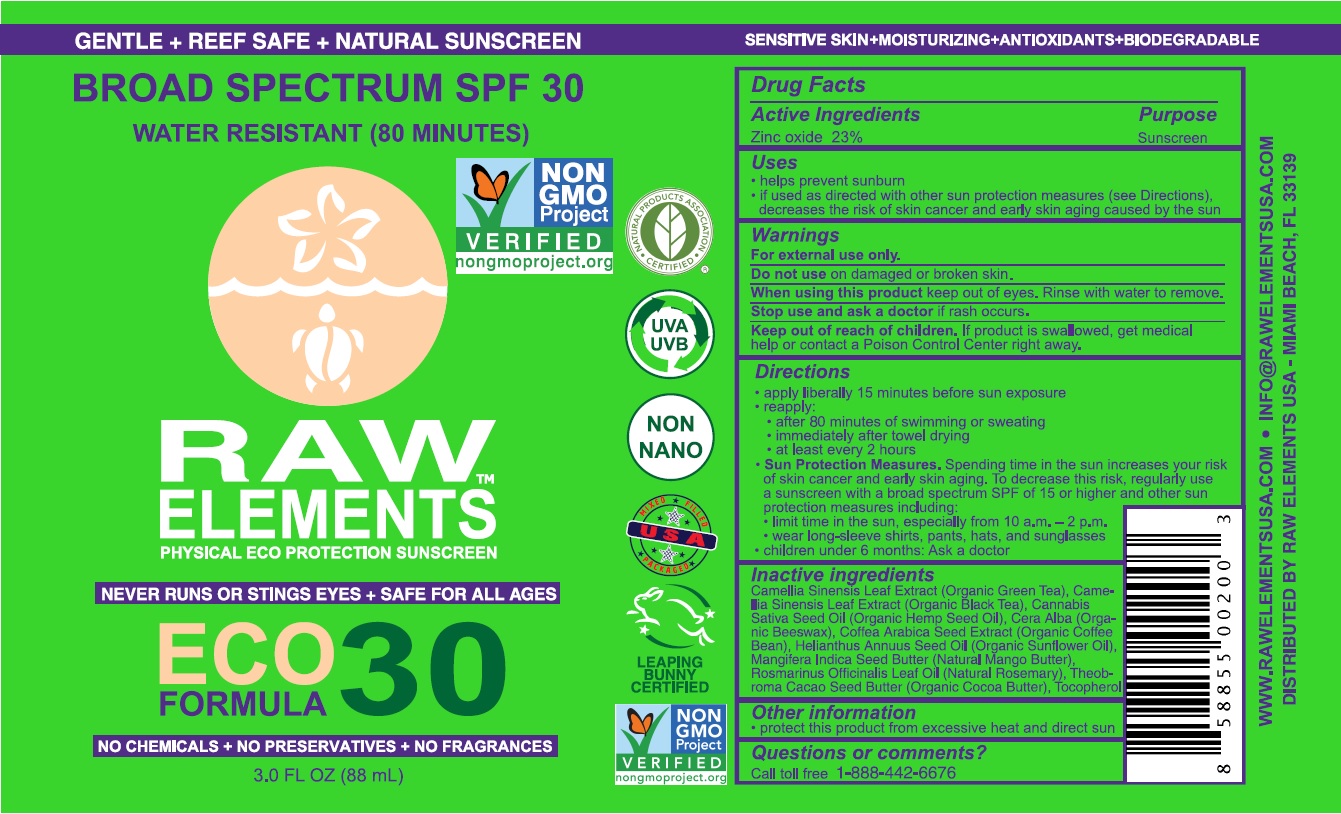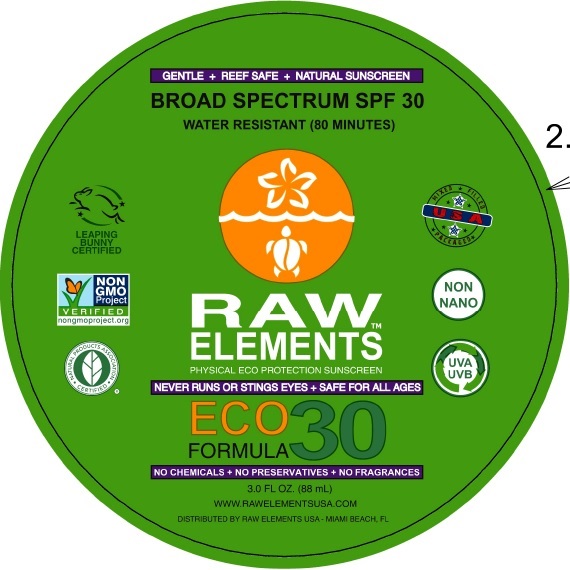 DRUG LABEL: Raw Elements Eco Formula 30 Broad Spectrum SPF 30
NDC: 70680-300 | Form: CREAM
Manufacturer: Raw Elements LLC
Category: otc | Type: HUMAN OTC DRUG LABEL
Date: 20231109

ACTIVE INGREDIENTS: ZINC OXIDE 230 mg/1 mL
INACTIVE INGREDIENTS: GREEN TEA LEAF; CANNABIS SATIVA SEED OIL; WHITE WAX; SUNFLOWER OIL; MANGIFERA INDICA SEED BUTTER; ROSEMARY OIL; TOCOPHEROL

Raw Elements Eco Formula 30 Broad Spectrum SPF 30

Active Ingredients

Zinc oxide 23%

Purpose

Sunscreen

Uses

- helps prevent sunburn
- if used as directed with other sun protection measures (see Directions), decreases the risk of skin cancer and early skin aging caused by the sun

Warnings

For external use only.

Do not use

on damaged or broken skin.

When using this product

keep out of eyes. Rinse with water to remove.

Stop use and ask a doctor

if rash occurs.

Keep out of reach of children.

If product is swallowed, get medical helps or contact a Poison Control Center right away.

Directions

• apply liberally 15 minutes before sun exposure • reapply

• after 80 minutes of swimming or sweating

• immediately after towel drying

• at least every 2 hours

• Sun Protection Measures. Spending time in the sun increases your risk of skin cancer and early skin aging. To decrease this risk, regularly use a sunscreen with a broad spectrum SPF of 15 or higher and other sun protection measures including:

• limit time in the sun especially from 10 a.m. - 2 p.m. • wear long-sleeve shirts, pants, hats, and sunglasses

• children under 6 months: Ask a doctor

Inactive ingredients

Camellia Sinensis Leaf Extract (Organic Green Tea), Camellia Sinensis Leaf Extract (Organic Black Tea), Cannabis Sativa Seed Oil (Organic Hemp Seed Oil), Cera Alba (Organic Beeswax), Coffea Arabica Seed Extract (Organic Coffee Bean), Helianthus Annuus Seed Oil (Organic Sunflower Oil), Mangifera Indica Seed Butter (Natural Mango Butter), Rosmarinus Officinalis Leaf Oil (Natural Rosemary), Theobroma Cacao Seed Butter (Organic Cocoa Butter), Tocopherol

Other information

• pretect this product from excessive heat and direct sun

Questions or comments?

Call toll free 1-888-442-6676